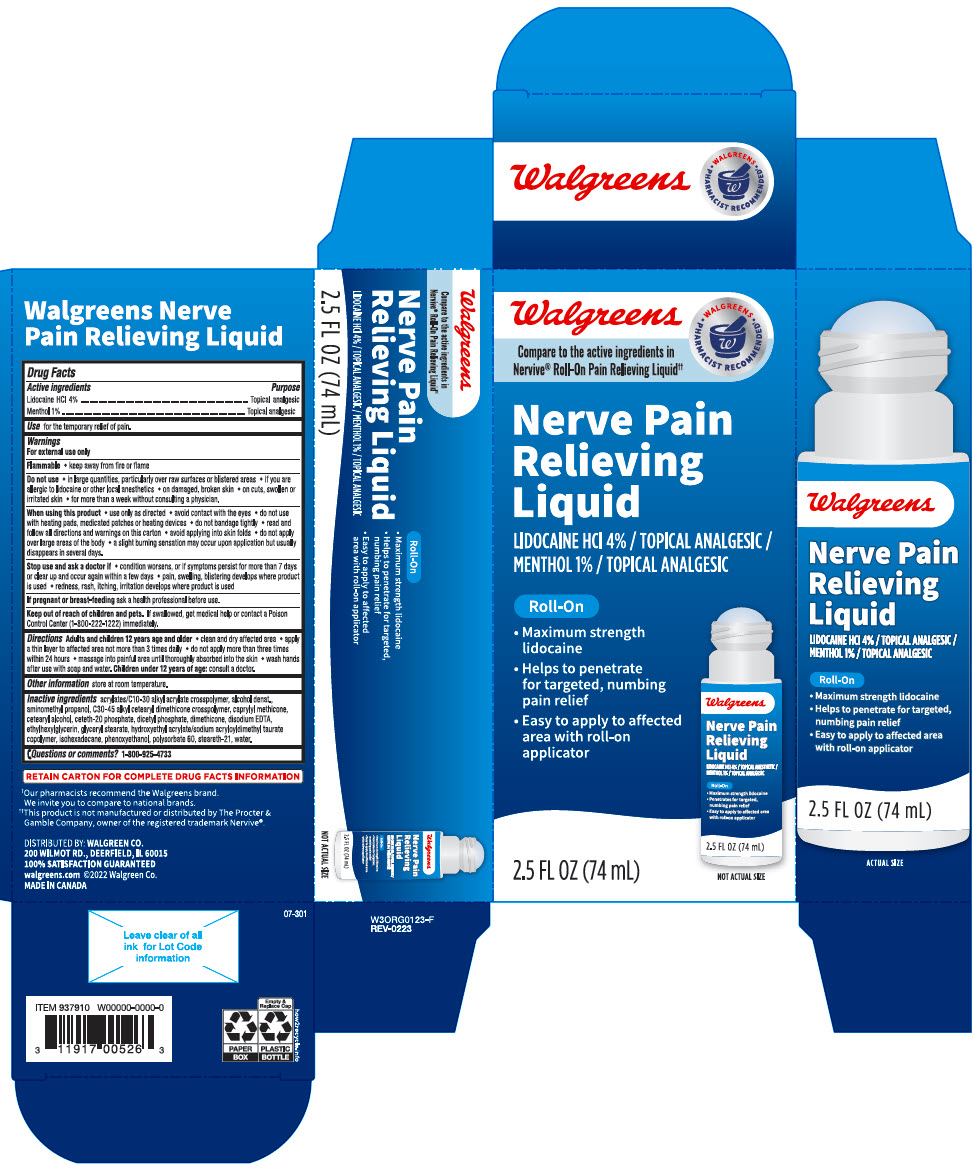 DRUG LABEL: Walgreens Nerve Pain Relieving
NDC: 0363-3791 | Form: LIQUID
Manufacturer: Walgreen Company
Category: otc | Type: HUMAN OTC DRUG LABEL
Date: 20241031

ACTIVE INGREDIENTS: Lidocaine Hydrochloride 40 mg/1 mL; Menthol, Unspecified Form 10 mg/1 mL
INACTIVE INGREDIENTS: Carbomer Interpolymer Type A (Allyl Sucrose Crosslinked); Alcohol; Aminomethylpropanol; C30-45 Alkyl Cetearyl Dimethicone Crosspolymer; Caprylyl Trisiloxane; Cetostearyl Alcohol; Ceteth-20 Phosphate; Dihexadecyl Phosphate; Dimethicone; Edetate Disodium Anhydrous; Ethylhexylglycerin; Glyceryl Monostearate; Hydroxyethyl Acrylate/Sodium Acryloyldimethyl Taurate Copolymer (100000 MPA.S AT 1.5%); Isohexadecane; Phenoxyethanol; Polysorbate 60; Steareth-21; Water

Walgreens Nerve Pain Relieving Liquid

ACTIVE INGREDIENT

Active ingredients | Purpose
Lidocaine HCl 4% | Topical analgesic
Menthol 1% | Topical analgesic

Use

for the temporary relief of pain.

Warnings

For external use only

Flammable

- keep away from fire or flame

Do not use

- in large quantities, particularly over raw surfaces or blistered areas
- if you are allergic to lidocaine or other local anesthetics
- on damaged, broken skin
- on cuts, swollen or irritated skin
- for more than a week without consulting a physician.

When using this product

- use only as directed
- avoid contact with the eyes
- do not use with heating pads, medicated patches or heating devices
- do not bandage tightly
- read and follow all directions and warnings on this carton
- avoid applying into skin folds
- do not apply over large areas of the body
- a slight burning sensation may occur upon application but usually disappears in several days.

Stop use and ask a doctor if

- condition worsens, or if symptoms persist for more than 7 days or clear up and occur again within a few days
- pain, swelling, blistering develops where product is used
- redness, rash, itching, irritation develops where product is used

PREGNANCY OR BREAST FEEDING

If pregnant or breast feeding ask a health professional before use.

Keep out of reach of children. If swallowed, get medical help or contact a Poison Control Center (1-800-222-1222) immediately.

Directions

Adults and children 12 years of age and older

- clean and dry affected area
- apply a thin layer to affected area not more than 3 times daily
- do not apply more than three times within 24 hours
- massage into painful area until thoroughly absorbed into the skin
- wash hands after use with soap and water.

Children under 12 years of age: consult a doctor.

Other information

store at room temperature

Inactive ingredients

acrylates/C10-30 alkyl acrylate crosspolymer, alcohol denat., aminomethyl propanol, C30-45 alkyl cetearyl dimethicone crosspolymer, caprylyl methicone, cetearyl alcohol, ceteth-20 phosphate, dicetyl phosphate, dimethicone, disodium EDTA, ethylhexylglycerin, glyceryl stearate, hydroxyethyl acrylate/sodium acryloyldimethyl taurate copolymer, isohexadecane, phenoxyethanol, polysorbate 60, steareth-21, water.

Questions or comments?

1-800-925-4733

DISTRIBUTED BY: WALGREEN CO.
200 WILMOT RD., DEERFIELD, IL 60015

PRINCIPAL DISPLAY PANEL - 74 mL Cylinder Carton

Walgreens
Compare to the active ingredients in
Nervive® Roll-On Pain Relieving Liquid††

WALGREENS
• PHARMACIST RECOMMENDED† •

Nerve Pain
Relieving
Liquid

LIDOCAINE HCl 4% / TOPICAL ANALGESIC /
MENTHOL 1% / TOPICAL ANALGESIC

Roll-On

- Maximum strength
  lidocaine
- Helps to penetrate
  for targeted, numbing
  pain relief
- Easy to apply to affected
  area with roll-on
  applicator

NOT ACTUAL SIZE

2.5 FL OZ (74 mL)